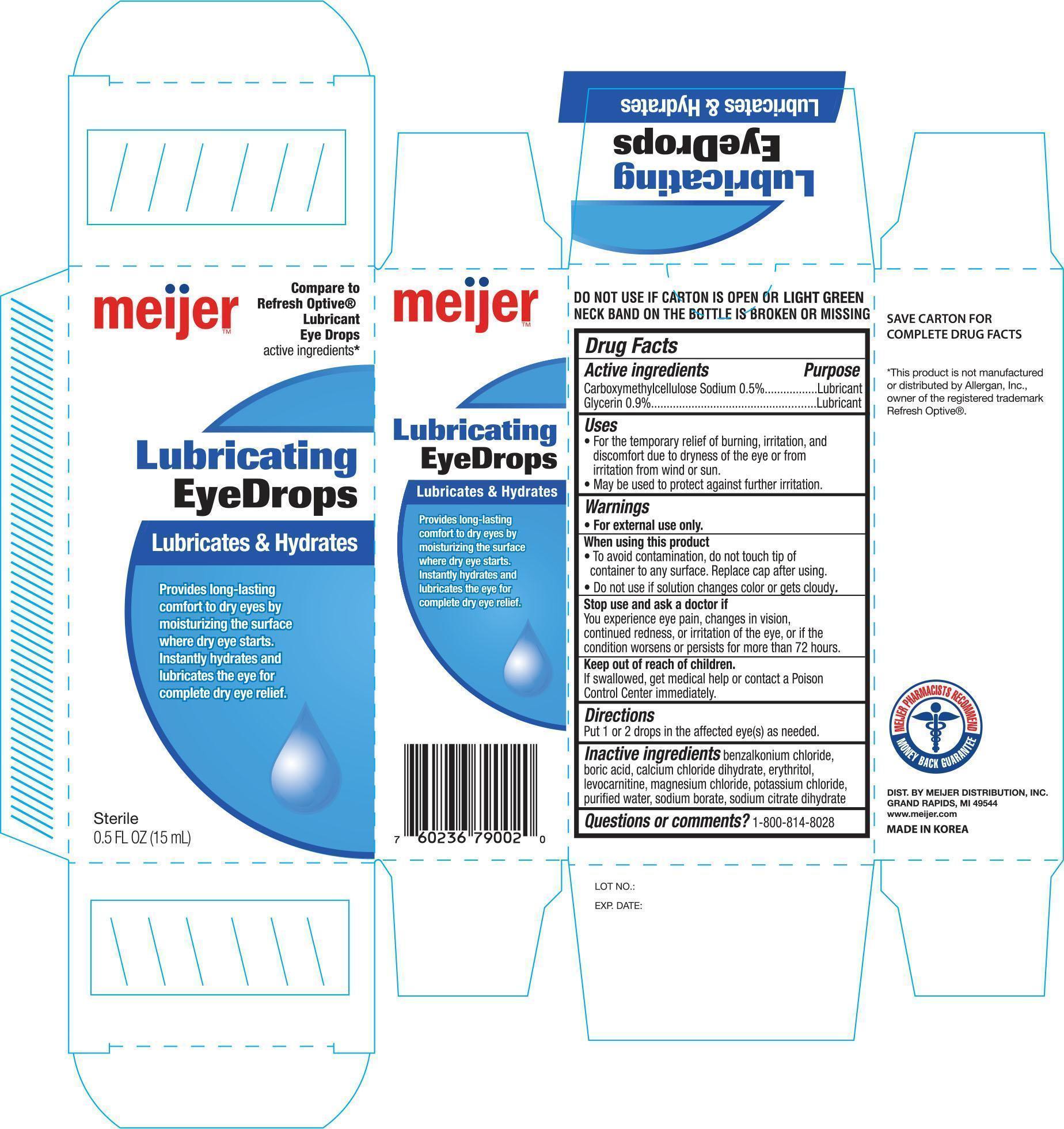 DRUG LABEL: Meijer Lubricating Eye
NDC: 41250-792 | Form: SOLUTION/ DROPS
Manufacturer: Meijer, Inc.
Category: otc | Type: HUMAN OTC DRUG LABEL
Date: 20150121

ACTIVE INGREDIENTS: CARBOXYMETHYLCELLULOSE SODIUM 5 mg/1 mL; GLYCERIN 9 mg/1 mL
INACTIVE INGREDIENTS: BENZALKONIUM CHLORIDE; BORIC ACID; CALCIUM CHLORATE DIHYDRATE; ERYTHRITOL; LEVOCARNITINE; MAGNESIUM CHLORIDE; POTASSIUM CHLORIDE; WATER; SODIUM BORATE

Active ingredients Purpose

Carboxymethylcellulose Sodium 0.5%....................................... Lubricant

Glycerin 0.9%........................................................................ Lubricant

Uses

- For the temporary relief of burning, irritation, and discomfort due to dryness of the eye or from irritation from win or sun.
- May be used to protect against futher irritation.

Warnings

- For external use only.

When using this product

- To avoid contamination, do not touch tip of container to any surface. Replace cap after using.
- Do not use if solution changes color or gets cloudy.

Stop use and ask a doctor if

You experience eye pain, changes in vision, continued redness, or irritation of the eye, or if the condition worsens or persists for more than 72 hours.

Keep out of reach of children.

If swallowed, get medical help or contact a Poison Control Center immediately.

Directions

Put 1 or 2 drops in the affected eye(s) as needed.

INACTIVE INGREDIENT

Inactive ingredients benzalkonium chloride, boric acid, calcium chloride dihydrate, erythritol, levocarnitine, magnesium chloride, potassium chloride, purified water, sodium borate, sodium citrate dihydrate

DOSAGE AND ADMINISTRATION

DISTRIBUTED BY:

MEIJER DISTRIBUTION INC.

GRAND RAPIDS, MI 49544

www.meijer.com

MADE IN KOREA